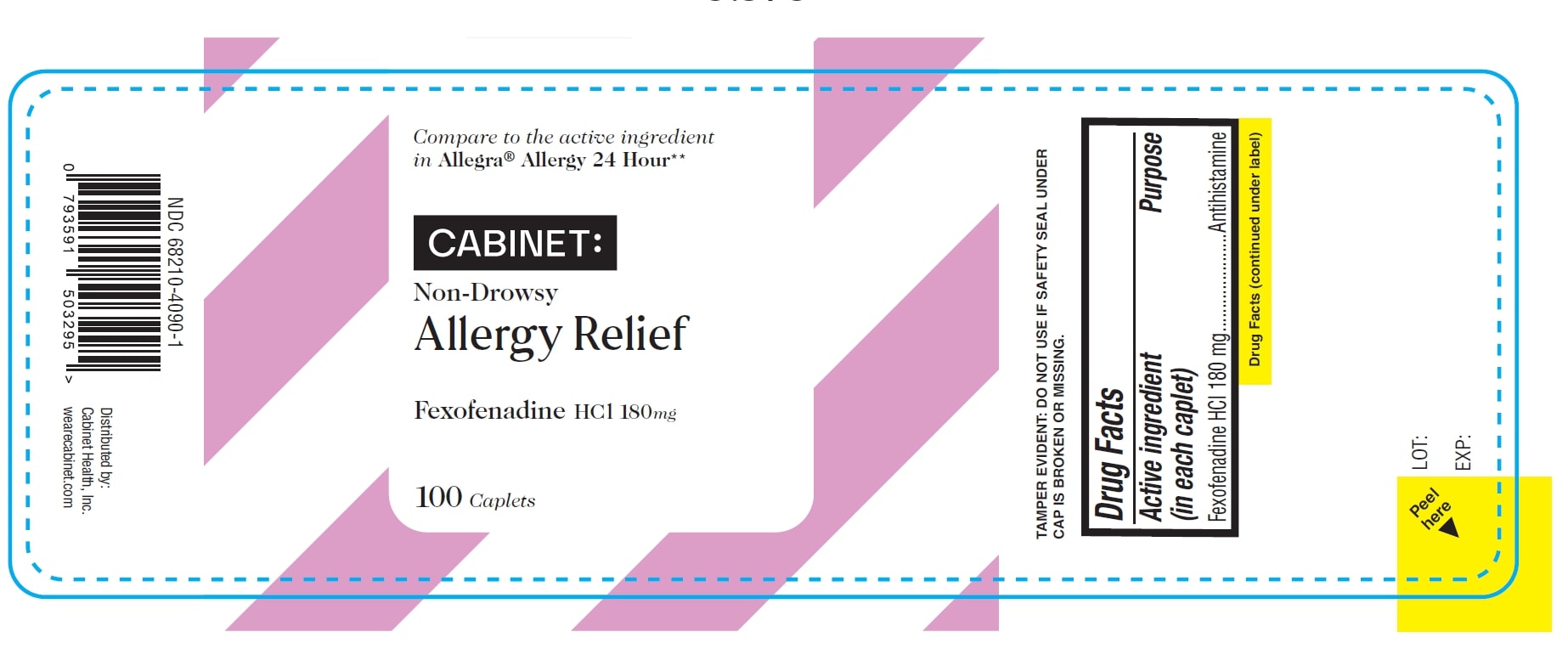 DRUG LABEL: Fexofenadine Hydrochloride
NDC: 68210-5034 | Form: TABLET, FILM COATED
Manufacturer: SPIRIT PHARMACEUTICALS LLC
Category: otc | Type: HUMAN OTC DRUG LABEL
Date: 20241213

ACTIVE INGREDIENTS: FEXOFENADINE HYDROCHLORIDE 180 mg/1 1
INACTIVE INGREDIENTS: SILICON DIOXIDE; CROSCARMELLOSE SODIUM; HYPROMELLOSE, UNSPECIFIED; FERRIC OXIDE RED; FERRIC OXIDE YELLOW; MAGNESIUM STEARATE; MICROCRYSTALLINE CELLULOSE; POLYETHYLENE GLYCOL, UNSPECIFIED; POVIDONE; STARCH, CORN; WATER; TITANIUM DIOXIDE

Fexofenadine Hydrochloride Tablets, 180 mg